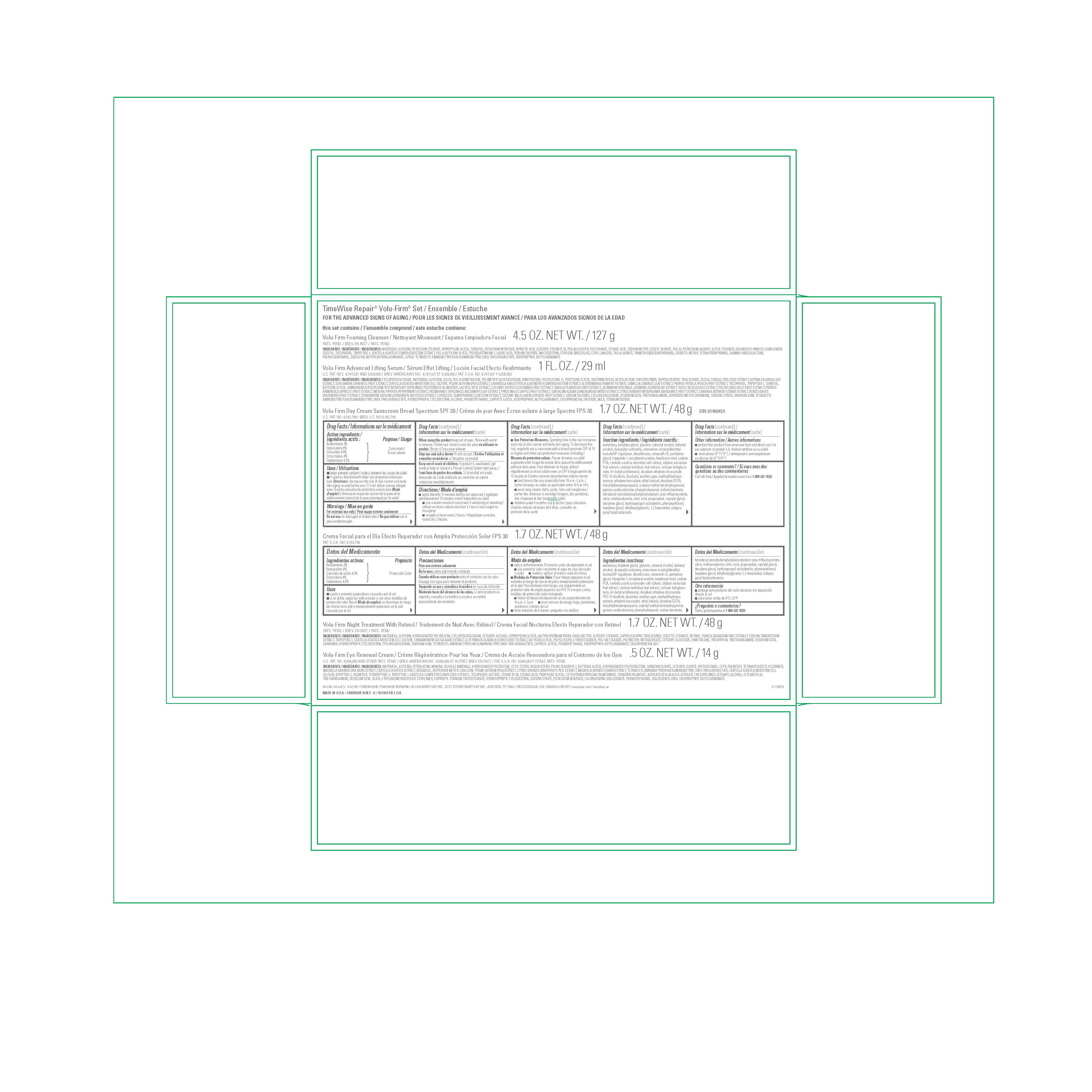 DRUG LABEL: Mary Kay TimeWise Repair Volu-Firm Set
NDC: 51531-8434 | Form: KIT | Route: TOPICAL
Manufacturer: Mary Kay Inc.
Category: otc | Type: HUMAN OTC DRUG LABEL
Date: 20241217

ACTIVE INGREDIENTS: AVOBENZONE 3 g/100 g; HOMOSALATE 9 g/100 g; OCTISALATE 4.5 g/100 g; OCTOCRYLENE 4 g/100 g; OXYBENZONE 4.5 g/100 g
INACTIVE INGREDIENTS: WATER; GLYCERIN; DIMETHICONE; BUTYLENE GLYCOL; CETOSTEARYL ALCOHOL; DOCOSANOL; DICAPRYLYL CARBONATE; AMMONIUM ACRYLOYLDIMETHYLTAURATE/VP COPOLYMER; CETEARETH-25; PENTYLENE GLYCOL; PHENOXYETHANOL; METHYL DIHYDROJASMONATE (SYNTHETIC); DISODIUM ETHYLENE DICOCAMIDE PEG-15 DISULFATE; CALCIUM 2-KETOGLUCONATE; HEXYLRESORCINOL; 4-TERT-BUTYLCYCLOHEXANOL; SILICON DIOXIDE; ETHYLENE BRASSYLATE; CAPRYLYL GLYCOL; EDETATE DISODIUM; ETHYL LINALOOL; TROLAMINE; LEVOMENOL; DECYLENE GLYCOL; .ALPHA.-TOCOPHEROL ACETATE; HYDROXYPROPYL .ALPHA.-CYCLODEXTRIN; 1,2-HEXANEDIOL; CENTELLA ASIATICA; ETHYLHEXYLGLYCERIN; HEXYLENE GLYCOL; SODIUM PYRROLIDONE CARBOXYLATE; TRIMETHYLBENZENEPROPANOL; 2-ISOBUTYL-4-METHYLTETRAHYDROPYRAN-4-OL; MILK THISTLE; .GAMMA.-UNDECALACTONE; CITRIC ACID MONOHYDRATE; PHENYLISOHEXANOL; PROPANEDIOL; IODOPROPYNYL BUTYLCARBAMATE; CESTRUM LATIFOLIUM LEAF; XANTHAN GUM; SODIUM BENZOATE; TETRADECYL AMINOBUTYROYLVALYLAMINOBUTYRIC UREA TRIFLUOROACETATE; PREZATIDE; MAGNESIUM CHLORIDE

Mary Kay
TimeWise Repair Volu-Firm Set
(Day Cream Rev 016)

Inactive ingredients

WATER, GLYCERIN, POTASSIUM STEARATE, DIPROPYLENE GLYCOL, SORBITOL, POTASSIUM MYRISTATE, MYRISTIC ACID, GLYCERYL STEARATE SE, PEG-60 GLYCERYL ISOSTEARATE, STEARIC ACID, SODIUM METHYL COCOYL TAURATE, PEG-32, POTASSIUM LAURATE, GLYCOL STEARATE, HELIANTHUS ANNUUS (SUNFLOWER) SEED OIL, TOCOPHEROL, TRIPEPTIDE-1, CENTELLA ASIATICA FLOWER/LEAF/STEM EXTRACT, PEG-6, BUTYLENE GLYCOL, POLYQUATERNIUM-7, LAURIC ACID, SODIUM CHLORIDE, MALTODEXTRIN, ETHYLENE BRASSYLATE, ETHYL LINALOOL, PEG-4 LAURATE, TRIMETHYLBENZENEPROPANOL, ISOBUTYL METHYL TETRAHYDROPYRANOL, GAMMA-UNDECALACTONE, PHENYLISOHEXANOL, SUBTILISIN, METHYLDIHYDROJASMONATE, LIPASE, TETRADECYL AMINOBUTYROYLVALYLAMINOBUTYRIC UREA TRIFLUOROACETATE, IODOPROPYNYL BUTYLCARBAMATE, SODIUM BENZOATE, MAGNESIUM CHLORIDE.

Inactive ingredients

CYCLOPENTASILOXANE, WATER, GLYCERIN, SILICA, PEG-10 DIMETHICONE, POLYMETHYLSILSESQUIOXANE, DIMETHICONE, POLYSILICONE-11, PENTYLENE GLYCOL, HDI/TRIMETHYLOL HEXYLLACTONE CROSSPOLYMER, CAPRYLIC/CAPRIC TRIGLYCERIDE, SECALE CEREALE (RYE) SEED EXTRACT, ALPINIA GALANGA LEAF EXTRACT, SCHISANDRA CHINENSIS FRUIT EXTRACT, CENTELLA ASIATICA MERISTEM CELL CULTURE, PISUM SATIVUM (PEA) EXTRACT, LAVANDULA ANGUSTIFOLIA (LAVENDER) FLOWER/LEAF/STEM EXTRACT, ALTEROMONAS FERMENT FILTRATE, CAMELLIA SINENSIS LEAF EXTRACT, PRUNUS PERSICA (PEACH) FRUIT EXTRACT, TOCOPHEROL, TRIPEPTIDE-1, SORBITOL, BUTYLENE GLYCOL, AMMONIUM ACRYLOYLDIMETHYLTAURATE/VP COPOLYMER, POLYSORBATE 40, MENTHYL LACTATE, ROSE EXTRACT, CUCUMIS SATIVUS (CUCUMBER) FRUIT EXTRACT, VANILLA PLANIFOLIA FRUIT EXTRACT, JASMINUM OFFICINALE (JASMINE) FLOWER/LEAF EXTRACT, FUCUS VESICULOSUS EXTRACT, PASSIFLORA EDULIS FRUIT EXTRACT, PRUNUS ARMENIACA (APRICOT) FRUIT EXTRACT, MENTHA PIPERITA (PEPPERMINT) EXTRACT, ROSMARINUS OFFICINALIS (ROSEMARY) LEAF EXTRACT, PYRUS MALUS (APPLE) FRUIT EXTRACT, SANTALUM ALBUM (SANDALWOOD) WOOD EXTRACT, CITRUS AURANTIUM BERGAMIA (BERGAMOT) FRUIT EXTRACT, CANANGA ODORATA FLOWER EXTRACT, RUBUS IDAEUS (RASPBERRY) FRUIT EXTRACT, CORIANDRUM SATIVUM (CORIANDER) FRUIT/LEAF EXTRACT, CUPRESSUS SEMPERVIRENS LEAF/STEM EXTRACT, CUCUMIS MELO CANTALUPENSIS FRUIT EXTRACT, SODIUM CHLORIDE, CYCLOHEXASILOXANE, DISODIUM EDTA, TRIETHANOLAMINE, DIHYDROXY METHYLCHROMONE, SODIUM CITRATE, XANTHAN GUM, TETRADECYL AMINOBUTYROYLVALYLAMINOBUTYRIC UREA TRIFLUOROACETATE, HYDROXYPROPYL CYCLODEXTRIN, ALCOHOL, PHENOXYETHANOL, CAPRYLYL GLYCOL, IODOPROPYNYL BUTYLCARBAMATE, CHLORPHENESIN, TIN OXIDE, MICA, TITANIUM DIOXIDE, CYCLODEXTRIN, MALTODEXTRIN, ALTEROMONAS FERMENT FILTRATE, MAGNESIUM CHLORIDE.

Volu-Firm Day Cream Sunscreen Broad-Spectrum SPF 30 1.7 OZ. NET WT. / 48 g

Drug Facts

Active ingredients

Avobenzone 3%

Homosalate 9%

Octisalate 4.5%

Octocrylene 4%

Oxybenzone 4.5%

Purpose

Sunscreen

Uses

- helps prevent sunburn
- if used as directed with other sun protection measures (see Directions), decreases the risk of skin cancer and early skin aging caused by the sun

Warnings

For external use only

Do not use

on damaged or broken skin

When using this product

keep out of eyes. Rinse with water to remove.

Stop use and ask a doctor

if rash occurs

Keep out of reach of children.

If product is swallowed, get medical help or contact a Poison Control Center right away.

Directions

- apply liberally 15 minutes before sun exposure
- use a water resistant sunscreen if swimming or sweating
- reapply at least every 2 hours
- Sun Protection Measures. Spending time in the sun increases your risk of skin cancer and early skin aging. To decrease this
  risk, regularly use a sunscreen with a broad spectrum SPF of 15 or higher and other sun protection measures including:
- limit time in the sun, especially from 10 a.m. - 2 p.m.
- wear long-sleeve shirts, pants, hats, and sunglasses
- children under 6 months: Ask a doctor

Inactive ingredients

water, butylene glycol, glycerin, cetearyl alcohol, behenyl alcohol, dicaprylyl carbonate, ammonium acryloyldimethyltaurate/VP copolymer, dimethicone, ceteareth-25, pentylene glycol, tripeptide-1, tocopheryl acetate, hexylresorcinol, sodium PCA, centella asiatica meristem cell culture, silybum marianum fruit extract, cestrum latifolium leaf extract, calcium ketogluconate, 4-t-butylcyclohexanol, disodium ethylene dicocamide PEG-15 disulfate, bisabolol, xanthan gum, methyldihydrojasmonate, ethylene brassylate, ethyl linalool, disodium EDTA, trimethylbenzenepropanol, isobutyl methyl tetrahydropyranol, gamma-undecalactone, phenylisohexanol, sodium benzoate, tetradecyl aminobutyroylvalylaminobutyric urea trifluoroacetate, silica, triethanolamine, citric acid, propanediol, caprylyl glycol, decylene glycol, hydroxypropyl cyclodextrin, phenoxyethanol, hexylene glycol, ethylhexylglycerin, 1,2-hexanediol, iodopropynyl butylcarbamate, magnesium chloride.

Other information

- protect this product from excessive heat and direct sun
- store below 32 F / 0 C

Questions or comments?

Call toll free 1-800-627-9529

INGREDIENTS:

WATER, GLYCERIN, HYDROGENATED POLYDECENE, CYCLOPENTASILOXANE, CETEARYL ALCOHOL, DIPROPYLENE GLYCOL, BUTYROSPERMUM PARKII (SHEA) BUTTER, GLYCERYL STEARATE, CAPRYLIC/CAPRIC TRIGLYCERIDE, ISOCETYL STEARATE, RETINOL, PUNICA GRANATUM FRUIT EXTRACT, CODIUM TOMENTOSUM EXTRACT, TRIPEPTIDE-1, CENTELLA ASIATICA MERISTEM CELL CULTURE, CINNAMOMUM CASSIA BARK EXTRACT, GLYCYRRHIZA GLABRA (LICORICE) ROOT EXTRACT, BUTYLENE GLYCOL, POLYGLYCERYL-2 TRIISOSTEARATE, PEG-100 STEARATE, POLYMETHYL METHACRYLATE, CETEARYL GLUCOSIDE, DIMETHICONE, TRICAPRYLIN, TRIETHANOLAMINE, DISODIUM EDTA, CARBOMER, HYDROXYPROPYL CYCLODEXTRIN, CYCLOHEXASILOXANE, XANTHAN GUM, TETRADECYL AMINOBUTYROYLVALYLAMINOBUTYRIC UREA TRIFLUOROACETATE, CAPRYLYL GLYCOL, PHENOXYETHANOL, IODOPROPYNYL BUTYLCARBAMATE, CHLORPHENESIN, BHT, MAGNESIUM CHLORIDE.

INGREDIENTS:

WATER, GLYCERIN, PETROLATUM, MINERAL OIL, HYDROGENATED POLYDECENE, CETYL ESTERS, BIS-DIGLYCERYL POLYACYLADIPATE-2, BUTYLENE GLYCOL, HYDROGENATED POLYISOBUTENE, SORBITAN OLIVATE, CETEARYL OLIVATE, HEXYLDECANOL, CETYL PALMITATE, TETRAHEXYLDECYL ASCORBATE, MAGNOLIA GRANDIFLORA BARK EXTRACT, CENTELLA ASIATICA EXTRACT, BISABOLOL, HESPERIDIN METHYL CHALCONE, PISUM SATIVUM (PEA) EXTRACT, CITRUS GRANDIS (GRAPEFRUIT) PEEL EXTRACT, MAGNOLIA BIONDII FLOWER EXTRACT, TETRADECYL AMINOBUTYROYLVALYLAMINOBUTYRIC UREA TRIFLUOROACETATE, CENTELLA ASIATICA MERISTEM CELL CULTURE, DIPEPTIDE-2, PALMITOYL TETRAPEPTIDE-7, TRIPEPTIDE-1, BRASSICA CAMPESTRIS (RAPESEED) STEROLS, TOCOPHERYL ACETATE, STEARETH-20, STEARIC ACID, PROPYLENE GLYCOL, CETYLHYDROXYPROLINE PALMITAMIDE, SORBITAN PALMITATE, ACRYLATES/C10-30 ALKYL ACRYLATE CROSSPOLYMER, CETEARYL ALCOHOL, CETEARETH-20, TRIETHANOLAMINE, DISODIUM EDTA, SILICA, ETHYLENE/METHACRYLATE COPOLYMER, ISOPROPYL TITANIUM TRIISOSTEARATE, HYDROXYPROPYL CYCLODEXTRIN, SODIUM CITRATE, POTASSIUM BENZOATE, CHLORHEXIDINE DIGLUCONATE, PHENOXYETHANOL, DIAZOLIDINYL UREA, IODOPROPYNYL BUTYLCARBAMATE, MAGNESIUM CHLORIDE.

Principal Display Panel - Repair Set carton

Mary Kay TimeWise Repair Volu-Firm Set

FOR THE ADVANCED SIGNS OF AGING

this set contains:

Volu-Firm Foaming Cleanser 4.5 OZ. NET WT. / 127 g

Volu-Firm Lifting Serum 1 FL. OZ. / 29 ml

Volu-Firm Day Cream Sunscreen Broad-Spectrum SPF 30 1.7 OZ. NET WT. / 48 g

Volu-Firm Night Treatment with Retinol 1.7 OZ. NET WT. / 48 g

Volu-Firm Eye Renewal Cream .5 OZ. NET WT. / 14 g